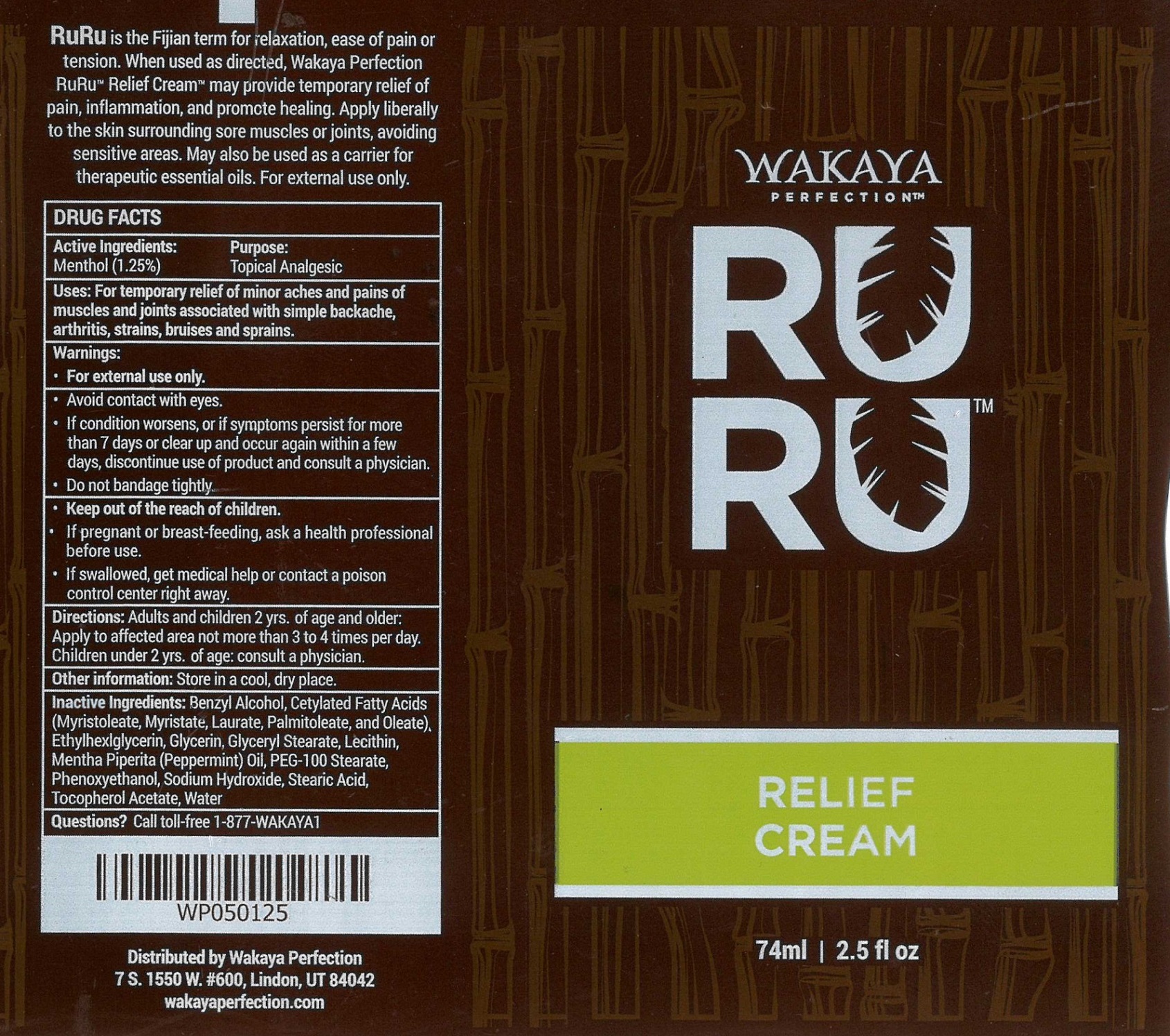 DRUG LABEL: Wakaya RuRu Topical Analgesic
NDC: 65112-265 | Form: CREAM
Manufacturer: I Shay Cosmetics Inc
Category: otc | Type: HUMAN OTC DRUG LABEL
Date: 20221018

ACTIVE INGREDIENTS: MENTHOL 1.25 g/100 g
INACTIVE INGREDIENTS: WATER 75 g/100 g

Wakaya RuRu Topical Analgesic

Active Ingredient

Menthol 1.25%..................... Topical Analgesic

PURPOSE

For the temporary relief of minor aches and pains of muscles and joints associated with simple backache, arthritis, strains, bruises, and sprains.

Keep Out of Reach of Children.

If pregnant or breast-feeding, ask a health professional before use.

If swallowed get medical help or contact poisoncontrol center right away.

Inactive Ingredients

Water

Cetylated Fatty Acids (Myristoleate, Myristate, Laurate, Palmitate, and Oleate)

Stearic Acid

Glyceryl Stearate

Glycerin

Benzyl Alcohol

Mentha Piperita (Peppermint Oil)

Lecithin

Phenoxyethanol

Sodium Hydroxide

Carbomer

Tocopheryl Acetate

Warnings

For external use only.

Avoid contact with eyes.

If condition worsens, or if symptoms persist for more than 7 days or clear up and occur again within a few days, discontinue use of product and consult a physician.

Do not bandage tightly

DIRECTIONS

Adults ands children 2 years of age and older: Apply to affected area not more than 3 to 4 times per day. Children under 2 years of age: Consult a physician

Other Information

Store in a cool, dry place.

INDICATIONS AND USAGE

For the temporary relief of minor aches and pains of muscles and joints associated with simple backache, arthritis, strains, bruises, and sprains.